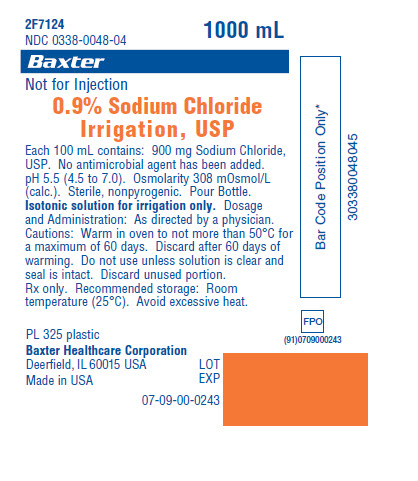 DRUG LABEL: SODIUM CHLORIDE
NDC: 0338-0048 | Form: IRRIGANT
Manufacturer: Baxter Healthcare Corporation
Category: prescription | Type: HUMAN PRESCRIPTION DRUG LABEL
Date: 20140221

ACTIVE INGREDIENTS: SODIUM CHLORIDE 900 mg/100 mL
INACTIVE INGREDIENTS: WATER

DESCRIPTION

0.9% Sodium Chloride Irrigation, USP

Each 100 mL contains: 900 mg Sodium Chloride, USP. No antimicrobial agent has been added. pH 5.5 (4.5 to 7.0). Osmolarity 308 mOsmol/L (calc.). Sterile, nonpyrogenic. Pour Bottle.

INDICATIONS AND USAGE

Isotonic solution for irrigation only. Not for injection.

DOSAGE AND ADMINISTRATION

As directed by a physician.

Cautions: Warm in oven to not more than 50°C for a maximum of 60 days. Discard after 60 days of warming. Do not use unless solution is clear and seal is intact. Discard unused portion. Rx only.

HOW SUPPLIED

Recommended storage: Room temperature (25°C). Avoid excessive heat.

PRINCIPAL DISPLAY PANEL - PACKAGING LABELING

Container Label

Container Label

2F7124
NDC 0338-0048-04

1000 mL

Baxter Logo

Not for Injection

0.9% Sodium Chloride Irrigation, USP

Each 100 mL contains: 900 mg Sodium
Chloride, USP. No antimicrobial agent has
been added. pH 5.5 (4.5 to 7.0). Osmolarity
308 mOsmol/L (calc.). Sterile, nonpyrogenic.
Pour Bottle. Isotonic solution for irrigation
only. Dosage and Administration: As
directed by a physician. Cautions: Warm in
oven to not more than 50°C for a maximum
of 60 days. Discard after 60 days of
warming. Do not use unless solution is clear
and seal is intact. Discard unused portion.
Rx only. Recommended storage: Room
temperature (25°C). Avoid excessive heat.

PL 325 plastic

Baxter Healthcare Corporation
Deerfield, IL 60015 USA

Made in USA

LOT
EXP

07-09-00-0243

Bar Code Position Only*
303380048045

FPO
(91)0709000243